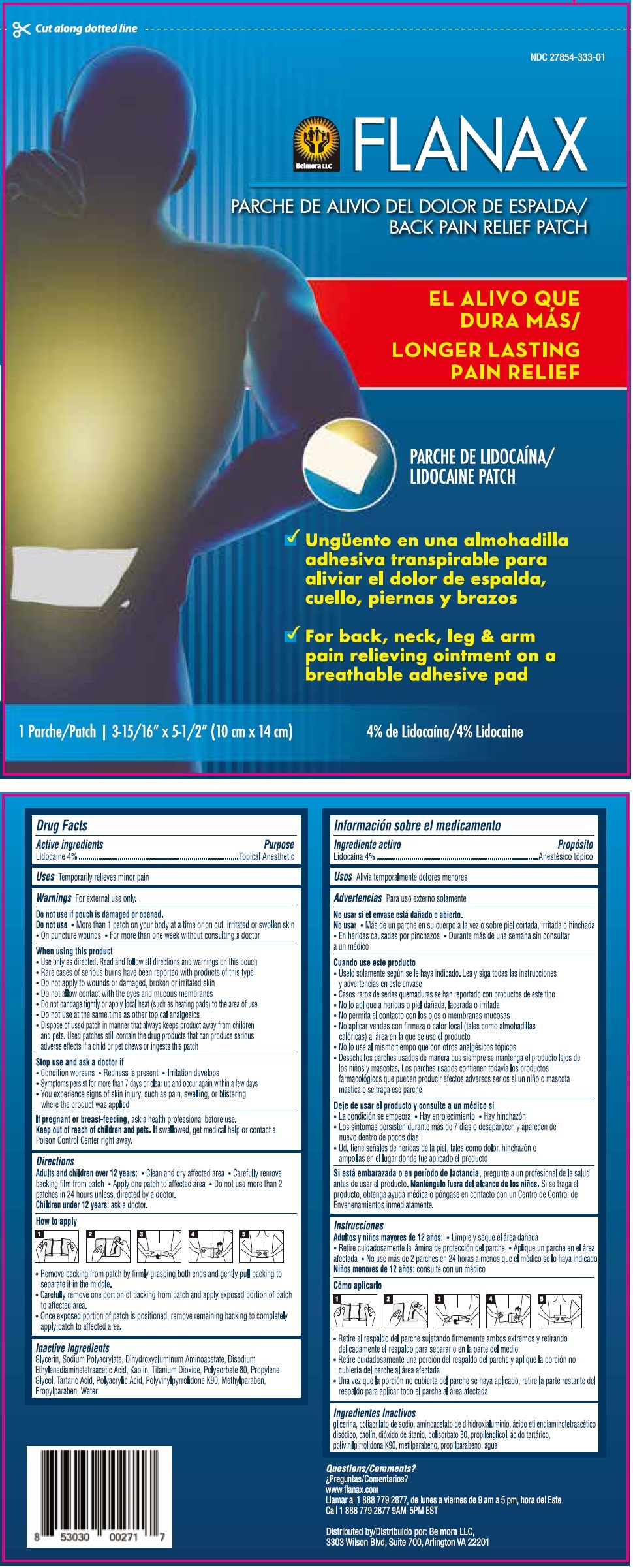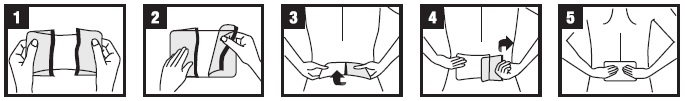 DRUG LABEL: Flanax Back Pain Relief
NDC: 27854-333 | Form: PATCH
Manufacturer: Belmora LLC
Category: otc | Type: HUMAN OTC DRUG LABEL
Date: 20241004

ACTIVE INGREDIENTS: LIDOCAINE 4 g/1 1
INACTIVE INGREDIENTS: GLYCERIN; SODIUM POLYACRYLATE (2500000 MW); DIHYDROXYALUMINUM AMINOACETATE; EDETATE DISODIUM; KAOLIN; TITANIUM DIOXIDE; POLYSORBATE 80; PROPYLENE GLYCOL; TARTARIC ACID; POLYACRYLIC ACID (250000 MW); POVIDONE K90; METHYLPARABEN; PROPYLPARABEN; WATER

FLANAX BACK PAIN RELIEF PATCH

Active ingredients

Lidocaine 4%

Purpose

Topical Anesthetic

Uses

Temporarily relieves minor pain

Warnings

For external use only.

Do not use if pouch is damaged or opened.

Do not use • More than 1 patch on your body at a time or on cut, irritated or swollen skin • On puncture wounds • For more than one week without consulting a doctor

When using this product
• Use only as directed. Read and follow all directions and warnings on this pouch
• Rare cases of serious burns have been reported with products of this type
• Do not apply to wounds or damaged, broken or irritated skin
• Do not allow contact with the eyes and mucous membranes
• Do not bandage tightly or apply local heat (such as heating pads) to the area of use
• Do not use at the same time as other topical analgesics
• Dispose of used patch in manner that always keeps product away from children and pets. Used patches still contain the drug products that can produce serious adverse effects if a child or pet chews or ingests this patch

Stop use and ask a doctor if
• Condition worsens • Redness is present • Irritation develops
• Symptoms persist for more than 7 days or clear up and occur again within a few days
• You experience signs of skin injury, such as pain, swelling, or blistering where the product was applied

If pregnant or breast-feeding, ask a health professional before use.

Keep out of reach of children and pets. If swallowed, get medical help or contact a Poison Control Center right away.

Directions

Adults and children over 12 years: • Clean and dry affected area • Carefully remove backing film from patch • Apply one patch to affected area • Do not use more than 2 patches in 24 hours unless, directed by a doctor.

Children under 12 years: ask a doctor.

How to apply

• Remove backing from patch by firmly grasping both ends and gently pull backing to separate it in the middle.
• Carefully remove one portion of backing from patch and apply exposed portion of patch to affected area.
• Once exposed portion of patch is positioned, remove remaining backing to completely apply patch to affected area.

Inactive Ingredients

Glycerin, Sodium Polyacrylate, Dihydroxyaluminum Aminoacetate, Disodium Ethylenediaminetetraacetic Acid, Kaolin, Titanium Dioxide, Polysorbate 80, Propylene Glycol, Tartaric Acid, Polyacrylic Acid, Polyvinylpyrrolidone K90, Methylparaben, Propylparaben, Water

LONGER LASTING PAIN RELIEF

• For back, neck, leg & arm pain relieving ointment on a breathable adhesive pad

Questions/Comments?
www.flanax.com
Call 1 888 779 2877 9AM-5PM EST

Distributed by: Belmora LLC
2011 Crystal Dr. Suite 400, Arlington, VA 22202